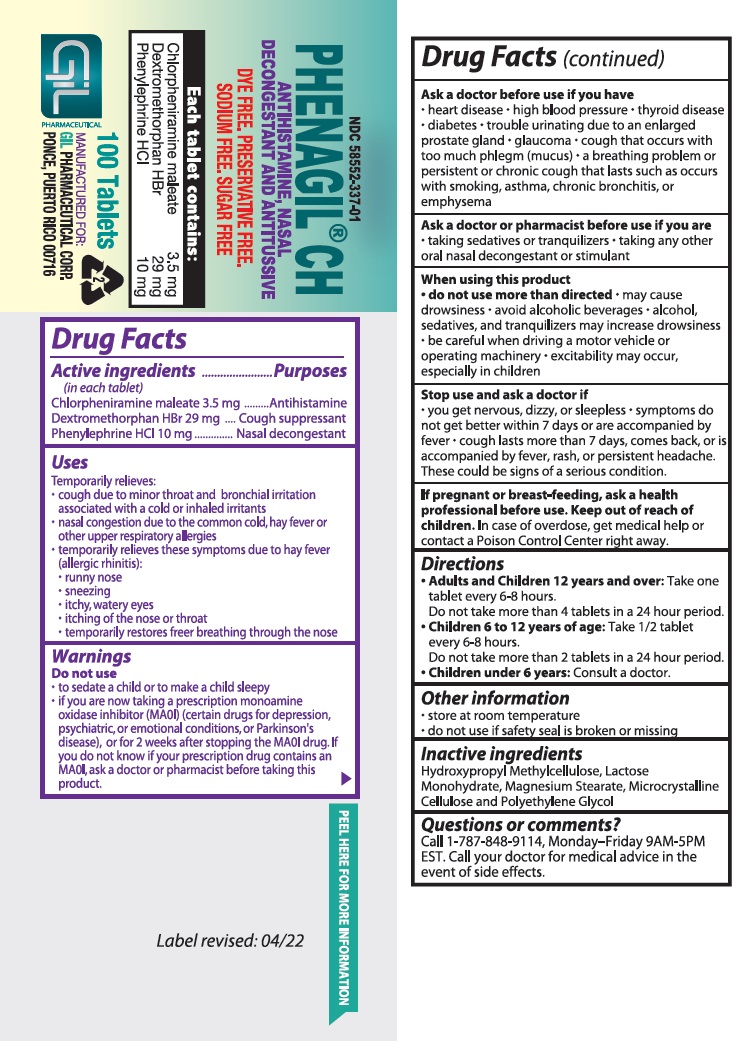 DRUG LABEL: PHENAGIL
NDC: 58552-337 | Form: TABLET
Manufacturer: Gil Pharmaceutical Corp.
Category: otc | Type: HUMAN OTC DRUG LABEL
Date: 20251009

ACTIVE INGREDIENTS: CHLORPHENIRAMINE MALEATE 3.5 mg/1 1; DEXTROMETHORPHAN HYDROBROMIDE 29 mg/1 1; PHENYLEPHRINE HYDROCHLORIDE 10 mg/1 1
INACTIVE INGREDIENTS: HYPROMELLOSE, UNSPECIFIED; LACTOSE MONOHYDRATE; MAGNESIUM STEARATE; MICROCRYSTALLINE CELLULOSE; POLYETHYLENE GLYCOL, UNSPECIFIED

PHENAGIL®CH
ANTIHISTAMINE, NASAL DECONGESTANT AND ANTITUSSIVE
DYE FREE
PRESERVATIVE FREE
SODIUM FREE
SUGAR FREE

Drug Facts

Active ingredients
(in each tablet)

Chlorpheniramine maleate 3.5 mg
Dextromethorphan HBr 29 mg
Phenylephrine HCI 10 mg

Purposes

Antihistamine
Cough suppressant
Nasal decongestant

Uses

Temporarily relieves:

• cough due to minor throat and bronchial irritation associated with a cold or inhaled irritants.

• nasal congestion due to the common cold, hay fever or other upper respiratory allergies.

• temporarily relieves these symptoms due to hay fever (allergic rhinitis):

• runny nose.

• sneezing.

• itchy, watery eyes.

• itching of the nose or throat.

• temporarily restores freer breathing through the nose.

Warnings

Do not use

• to sedate a child or to make a child sleepy.
• if you are now taking a prescription monoamine oxidase inhibitor (MAOI) (certain drugs for depression, psychiatric, or emotional conditions, or Parkinson's disease), or for 2 weeks after stopping the MAOI drug. If you do not know if your prescription drug contains an MAOI, ask a doctor or pharmacist before taking this product.

Ask a doctor before use if you have

• heart disease.
• high blood pressure.
• thyroid disease.
• diabetes.
• trouble urinating due to an enlarged prostate gland.
• glaucoma.
• cough that occurs with too much phlegm (mucus).
• a breathing problem or persistent or chronic cough that lasts such as occurs with smoking, asthma, chronic bronchitis, or emphysema.

Ask a doctor or pharmacist before use if you are

• taking sedatives or tranquilizers.
• taking any other oral nasal decongestant or stimulant.

When using this product

• do not use more than directed.
• may cause drowsiness.
• avoid alcoholic beverages.
• alcohol, sedatives, and tranquilizers may increase drowsiness.
• be careful when driving a motor vehicle or operating machinery.
• excitability may occur, especially in children.

Stop use and ask a doctor if

• you get nervous, dizzy, or sleepless.
• symptoms do not get better within 7 days or are accompanied by fever.
• cough lasts more than 7 days, comes back, or is accompanied by fever, rash, or persistent headache. These could be signs of a serious condition.

KEEP OUT OF REACH OF CHILDREN

If pregnant or breast-feeding, ask a health professional before use. Keep out of reach of children.In case of overdose, get medical help or contact a Poison Control Center right away.

Directions

• Adults and Children 12 years and over.: Take one tablet every 6-8 hours.
Do not take more than 4 tablets in a 24 hour period.
• Children 6 to 12 years of age: Take 1/2 tablet every 6-8 hours.
Do not take more than 2 tablets in a 24 hour period.
• Children under 6 years: Consult a doctor.

Other information

• store at room temperature.
• do not use if safety seal is broken or missing.

Inactive ingredients

Hydroxypropyl Methylcellulose, Lactose Monohydrate, Microcrystalline Cellulose, Magnesium Stearate and Polyethylene Glycol.

Questions or comments?

Call 1-787-848-9114,Monday–Friday 9AM-5PM EST. Call your doctor for medical advice in the event of side effects.
MANUFACTURED FOR:
GIL PHARMACEUTICAL CORP.
PONCE, PUERTO RICO 00716
Label revised: 04/22

PACKAGE LABEL.PRINCIPAL DISPLAY PANEL

PHENAGIL® CH - NDC 58552-337-01 - 100's Bottle Label.